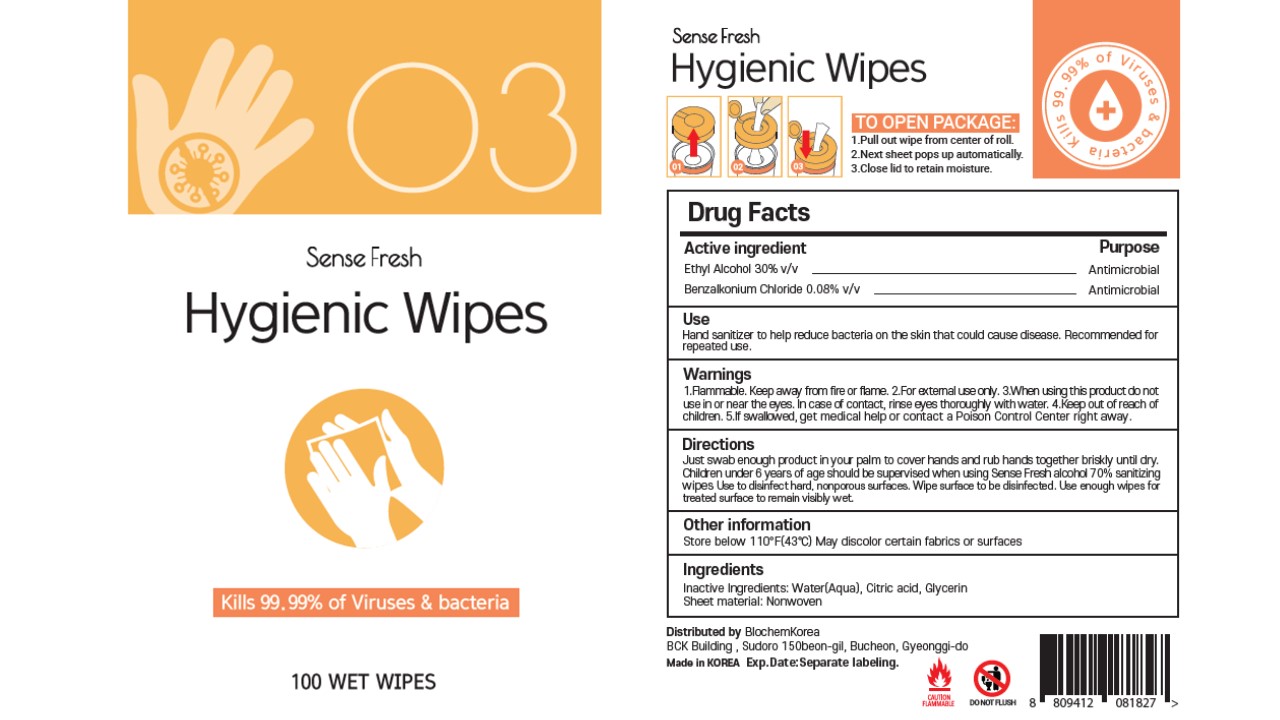 DRUG LABEL: SENSE FRESH
NDC: 74085-0011 | Form: LIQUID
Manufacturer: BIOCHEM KOREA CO., LTD
Category: otc | Type: HUMAN OTC DRUG LABEL
Date: 20210113

ACTIVE INGREDIENTS: ALCOHOL 150 g/500 g; BENZALKONIUM CHLORIDE 0.4 g/500 g
INACTIVE INGREDIENTS: ANHYDROUS CITRIC ACID; GLYCERIN; WATER

Warnings

1. Flammable. Keep away from fire or flame. 2. For external use only. 3. When using this product, do not use in or near the eyes. In case of contact, rinse eyes thoroughly with water.4. Keep out of reach of children. 5. If swallowed, get medical help or contact a Poison Control Center right away.

Active Ingredients

Ethyl Alcohol 30% v/v Antimicrobial

Benzalkonium Chloride 0.08% v/v Antimicrobial

Keep out of reach of children

Children under 6 years of age should be supervised when using Sense Fresh Hygienic Wipes.

Do not use

When using this product, do not use in or near the eyes.

In case of contact, rinse eyes thoroughly with water.

Ask doctors

If swallowed, get medical help or contact a Poison Control Center right away.

Use

Hand sanitizer to help reduce bacteria and viruses on the skin that could cause disease.

Recommended for repeated use.

Other Information

Store below 110°F (43°C). May discolor certain fabrics or surfaces.